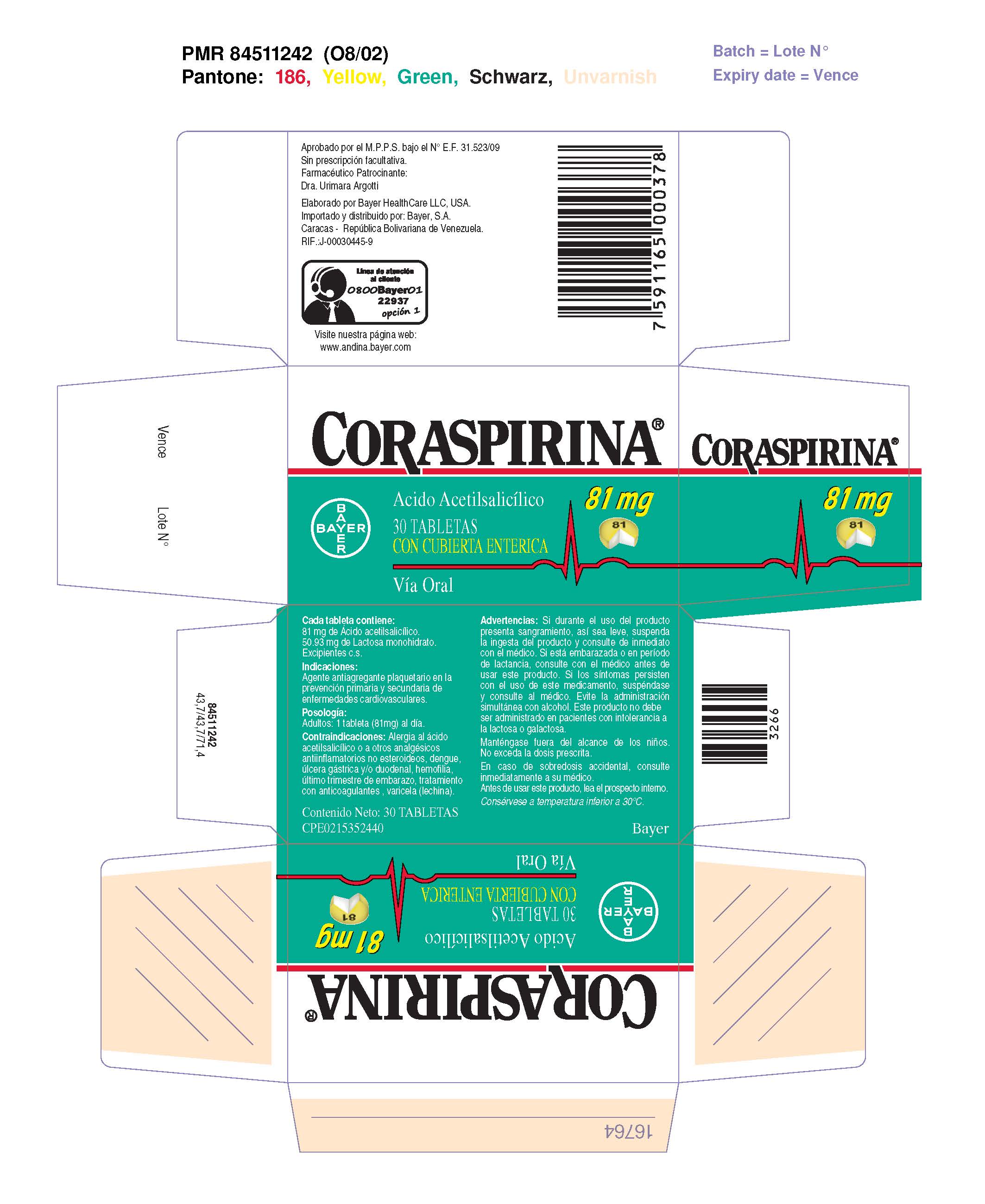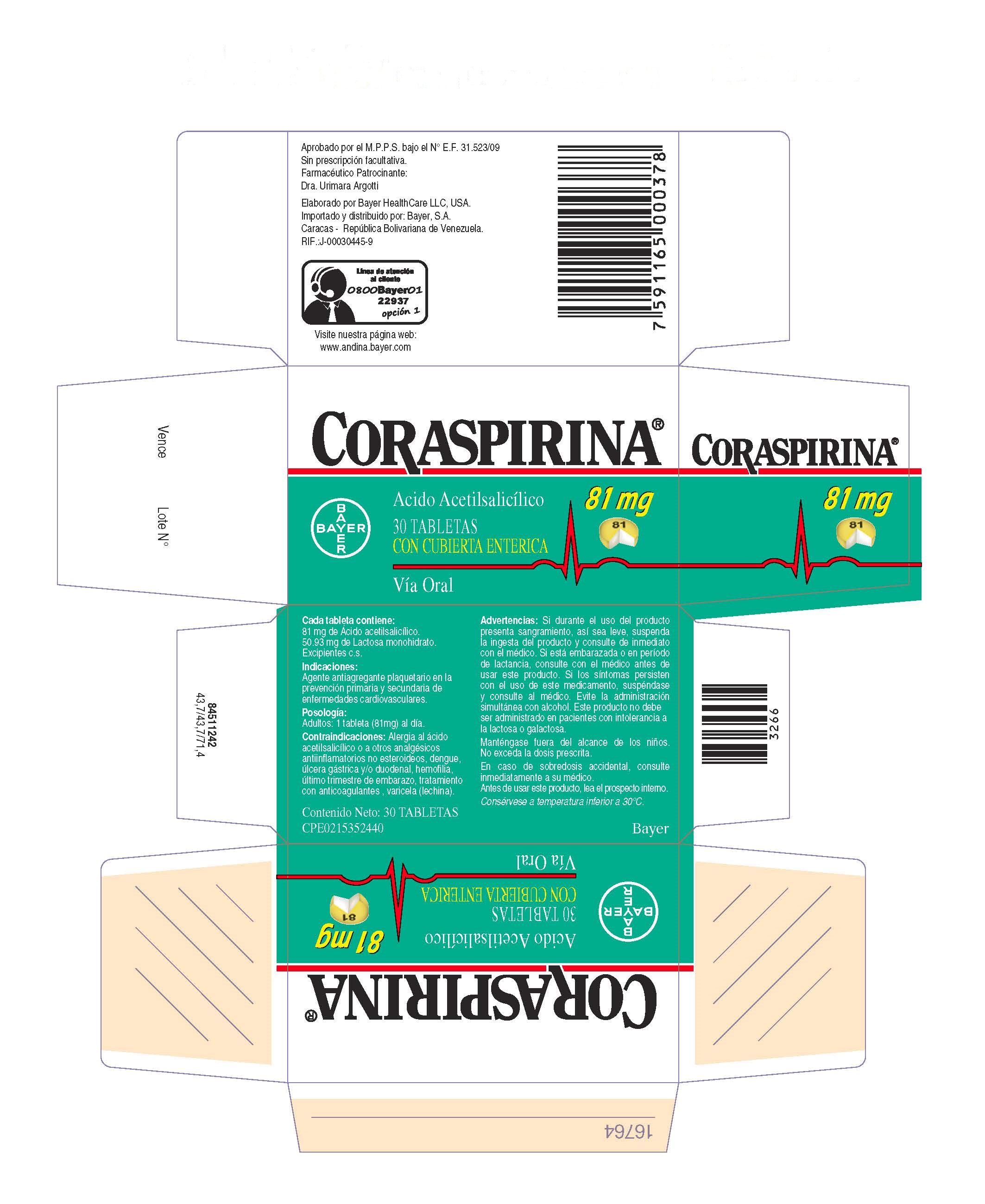 DRUG LABEL: Coraspirina 81 mg Tabletas con cubierta enterica
NDC: 0280-2055 | Form: TABLET, COATED
Manufacturer: Bayer HealthCare LLC.
Category: otc | Type: HUMAN OTC DRUG LABEL
Date: 20250117

ACTIVE INGREDIENTS: ASPIRIN 81 mg/1 1
INACTIVE INGREDIENTS: BROWN IRON OXIDE; POWDERED CELLULOSE; LACTOSE MONOHYDRATE; STARCH, CORN; D&C YELLOW NO. 10; HYPROMELLOSES; METHACRYLIC ACID - ETHYL ACRYLATE COPOLYMER (1:1) TYPE A; POLYSORBATE 80; ALUMINUM OXIDE; FD&C YELLOW NO. 6; SODIUM LAURYL SULFATE; FERROSOFERRIC OXIDE; CARNAUBA WAX; SHELLAC; PROPYLENE GLYCOL; TRIACETIN; TRIETHYL CITRATE

Coraspirina 81 mg Tabletas concubierta enterica